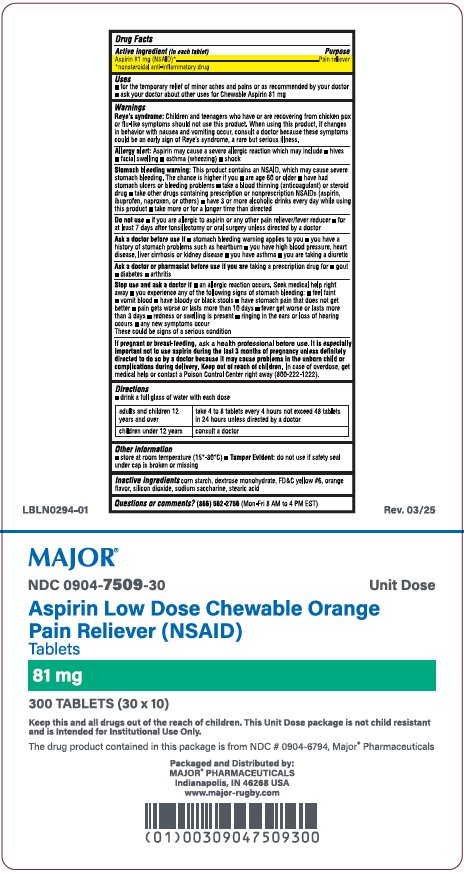 DRUG LABEL: Aspirin Low Dose Chewable Orange
NDC: 0904-7509 | Form: TABLET, CHEWABLE
Manufacturer: Major Pharmaceuticals
Category: otc | Type: HUMAN OTC DRUG LABEL
Date: 20260123

ACTIVE INGREDIENTS: ASPIRIN 81 mg/1 1
INACTIVE INGREDIENTS: STARCH, CORN; DEXTROSE MONOHYDRATE; FD&C YELLOW NO. 6; SILICON DIOXIDE; SACCHARIN SODIUM; STEARIC ACID

Drug Facts

Active ingredient (in each tablet)

Aspirin 81mg (NSAID)*

*nonsteroidal anti-inflammatory drug

Purpose

Pain reliever

Uses

- for the temporary relief of minor aches and pains or as recommneded by your doctor
- ask your doctor about other uses for Chewable Aspirin 81 mg

Warnings

Reye's syndrome: Children and teenagers who have or are recovering from chicken pox or flu-like symptoms should not use this product. When using this product, if changes in behavior with nausea and vomiting occur, consult a doctor because these symptoms could be an early sign of Reye's syndrome, a rare but serious illness.

Allergy alert: Aspirin may cause a severe allergic reaction which may include

- hives
- facial swelling
- asthma (wheezing)
- shock

Stomach bleeding warning: This product contains an NSAID, which may cause severe stomach bleeding. The chance is higher if you

- are age 60 or older
- have had stomach ulcers or bleeding problems
- take a blood thinning (anticoagulant) or steroid drug
- take other drugs containing prescription or nonprescription NSAIDs (aspirin, ibuprofen, naproxen, or others)
- have 3 or more alcoholic drinks every day while using this product
- take more or for a longer time than directed

Do not use

- if you are allergic to aspirin or any other pain reliever/fever reducer
- for at least 7 days after tonsillectomy or oral surgery unless directed by a doctor

Ask a doctor before use if

- stomach bleeding warning applies to you
- you have a history of stomach problems such as heartburn
- you have high blood pressure, heart disease, liver cirrhosis or kidney disease
- you have asthma
- you are taking a diuretic

Ask a doctor or pharmacist before use if you are

taking a prescription drug for

- gout
- diabetes
- arthritis

Stop use and ask a doctor if

- an allergic reaction occurs. Seek medical help right away.
- you experience any of the following signs of stomach bleeding:
- feel faint
- vomit blood
- have bloody or black stools
- have stomach pain that does not get better
- pain gets worse or lasts more than 10 days
- fever get worse or lasts more than 3 days
- redness or swelling is present
- ringing in the ears or loss of hearing occurs
- any new symptoms occur

These could be signs of a serious condition

If pregnant or breast-feeding

ask a health professional before use. It is especially important not to use aspirin during the last 3 months of pregnancy unless definitely directed to do so by a doctor because it may cause problems in the unborn child or complications during delivery.

Keep out of reach of children.

In case of accidental overdose, get medical help or contact a Poison Control Center right away. (800-222-1222).

Directions

- drink a full glass of water with each dose

adults and children 12 years and over | take 4 to 8 tablets every 4 hours not exceed 48 tablets in 24 hours unless directed by a doctor
children under 12 years | consult a doctor

Other information

- store at room temperature (15^0-30^0C)
- Tamper Evident: do not use if safety seal under cap is broken or missing

Inactive ingredients

corn starch, dextrose monohydrate, FD&C yellow #6, orange flavor, silicon dioxide, sodium saccharine, stearic acid

Questions or comments?

(866) 562-2756 (Mon-Fri 8 AM to 4 PM EST)

.

Cartons of 300 chewable tablets (10 chewable tablets each blister pack x 30), NDC 0904-7509-30

WARNING: This Unit Dose package is not child resistant and is Intended for Institutional Use Only. Keep this and all drugs out of the reach of children.

Packaged and Distributed by:

MAJOR® PHARMACEUTICALS

Indianapolis, IN 46268 USA

Refer to package label for Distributor's NDC Number

Rev. 12/23 | Re-order No. 701003 | M-111

Principal Display Panel

MAJOR®

0904-7509-30

Unit Dose

Aspirin Low Dose Chewable Orange

Pain Reliever (NSAID)

Tablets

81 mg

300 TABLETS (30 x 10)

Keep this and all drugs out of the reach of children. This Unit Dose package is not child resistant

and is Intended for Institutional se Only.

The drug product contained in this package is from NDC # 0904-6794, Major® Pharmaceuticals

Packaged and Distributed by:

MAJOR® PHARMACEUTICALS

Indianapolis, IN 46268 USA

www.major-rugby.com